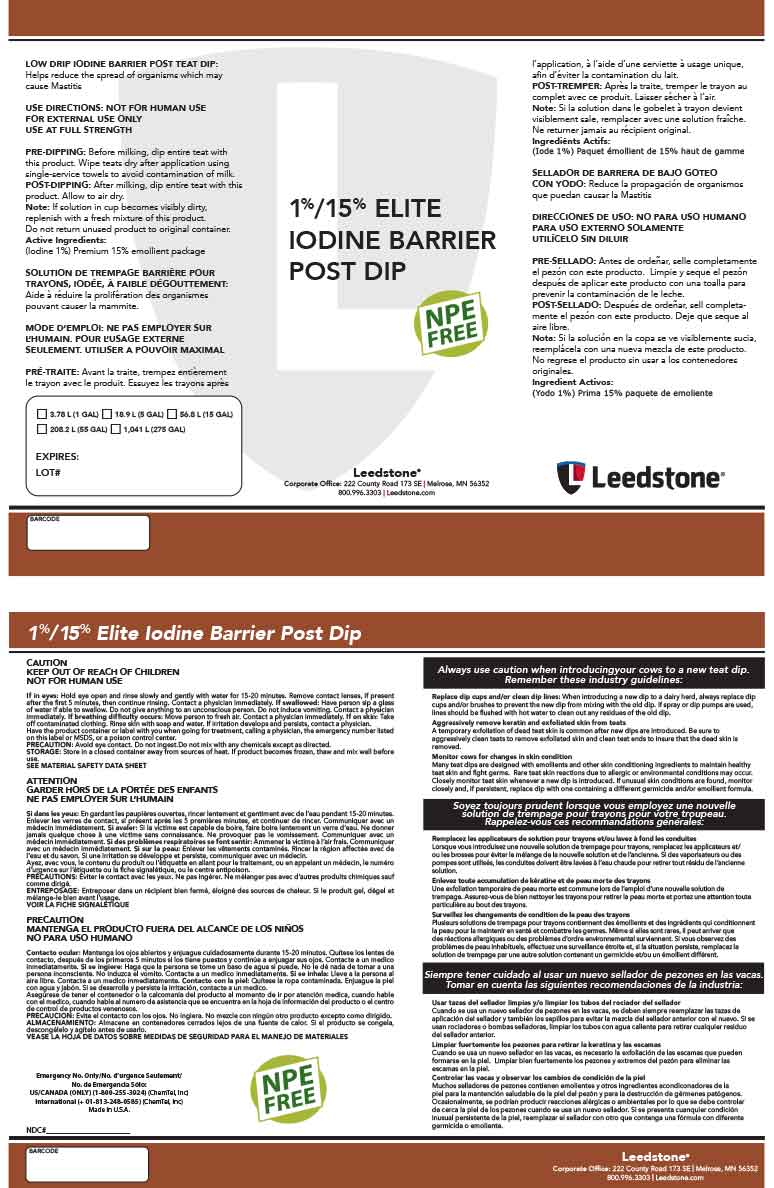 DRUG LABEL: 1%/15% Elite Iodine Barrier Post Dip
NDC: 48106-2045 | Form: LIQUID
Manufacturer: BOUMATIC, LLC
Category: animal | Type: OTC ANIMAL DRUG LABEL
Date: 20221202

ACTIVE INGREDIENTS: IODINE 1 g/100 g
INACTIVE INGREDIENTS: GLYCERIN 6 g/100 g; SORBITOL 2.38 g/100 g; PROPYLENE GLYCOL 3 g/100 g; WATER 87.62 g/100 g

1%/15% Elite Iodine Barrier Post Dip

Summary of effectiveness

Helps reduce the spread of organisms which
may cause Mastitis

Instructinos for use

USE DIRECTIONS: NOT FOR HUMAN USE
FOR EXTERNAL USE ONLY
USE AT FULL STRENGTH
PRE-DIPPING: Before milking, dip entire teat with
this product. Wipe teats dry after application using
single-service towels to avoid contamination of milk.
POST-DIPPING: After milking, dip entire teat with this
product. Allow to air dry.
Note: If solution in cup becomes visibly dirty,
replenish with a fresh mixture of this product.
Do not return unused product to original container.

Safe Handling

CAUTION
KEEP OUT OF REACH OF CHILDREN
NOT FOR HUMAN USE

General Precautions

Avoid eye contact. Do not ingest.Do not mix with any chemicals except as directed.

NOT FOR HUMAN USE
FOR EXTERNAL USE ONLY
USE AT FULL STRENGTH

Storage

Store in a closed container away from sources of heat. If product becomes frozen, thaw and mix well before
use.

Label